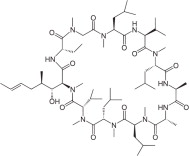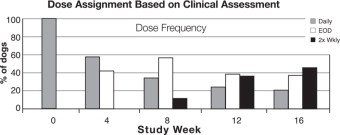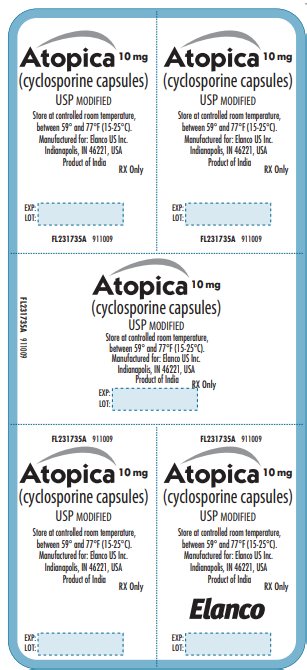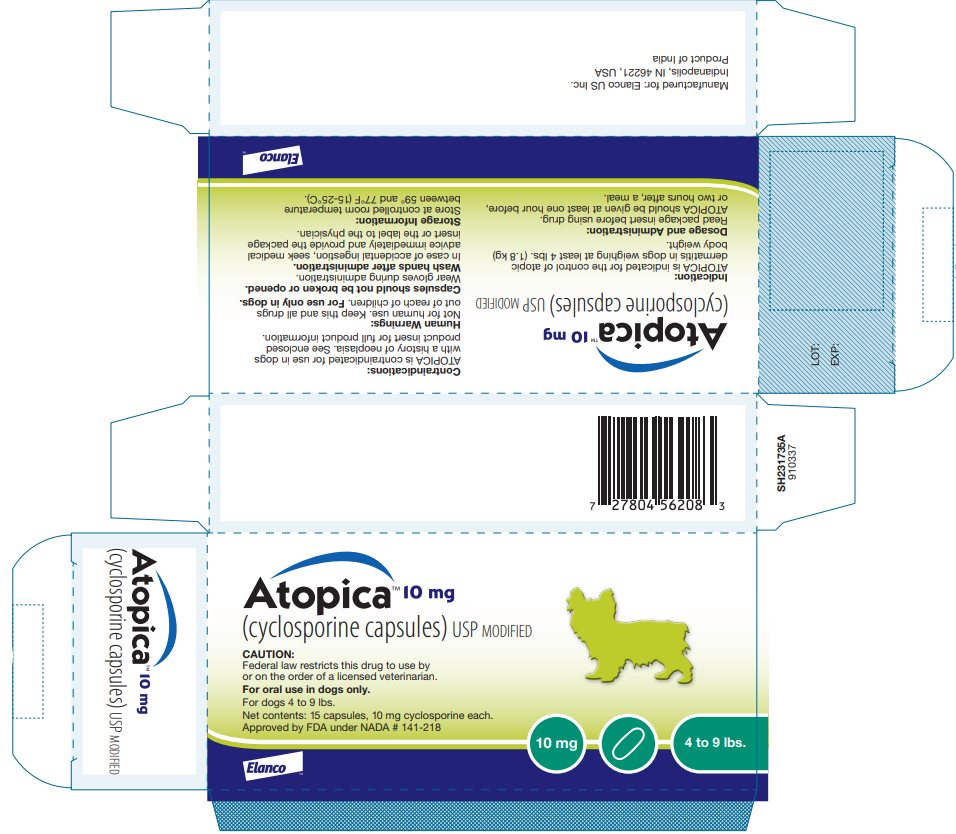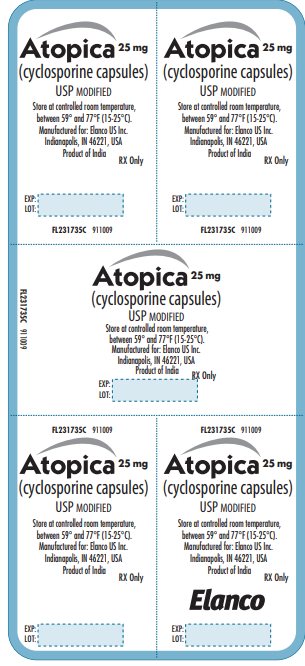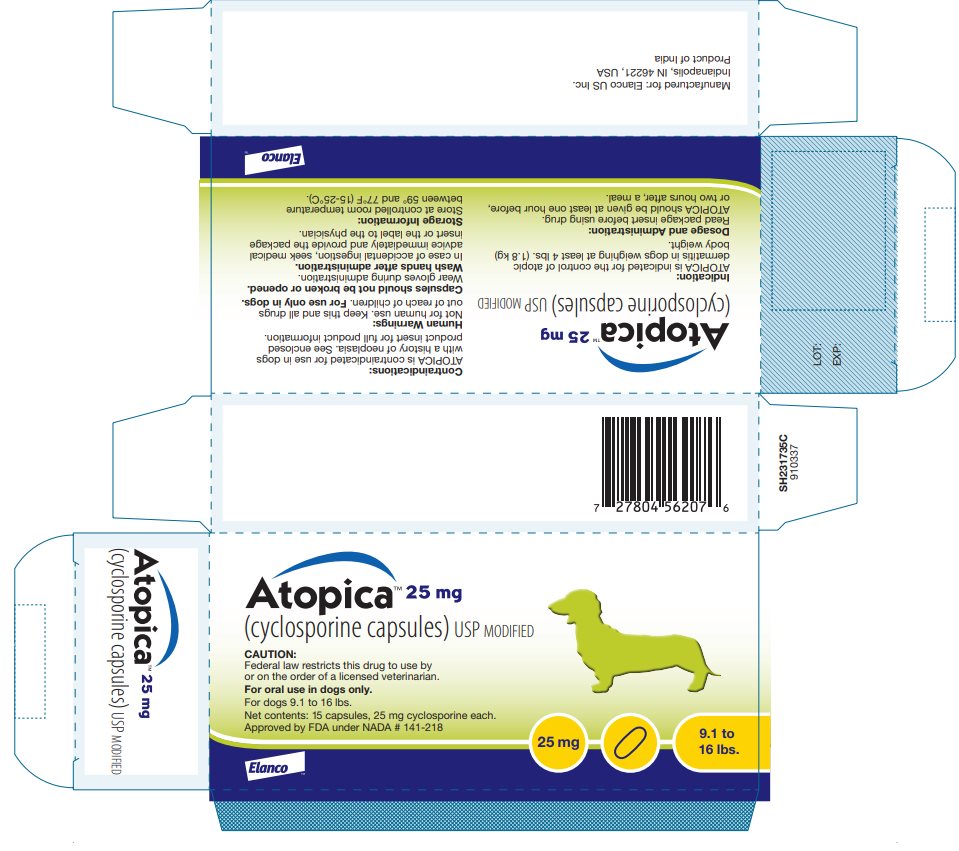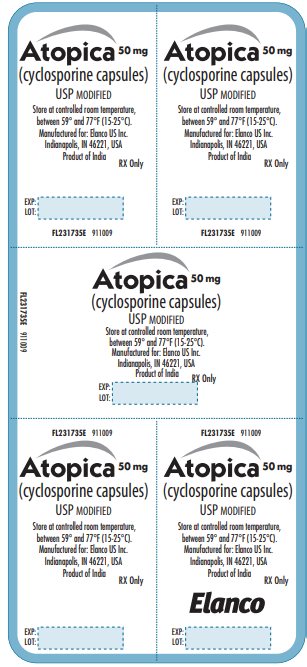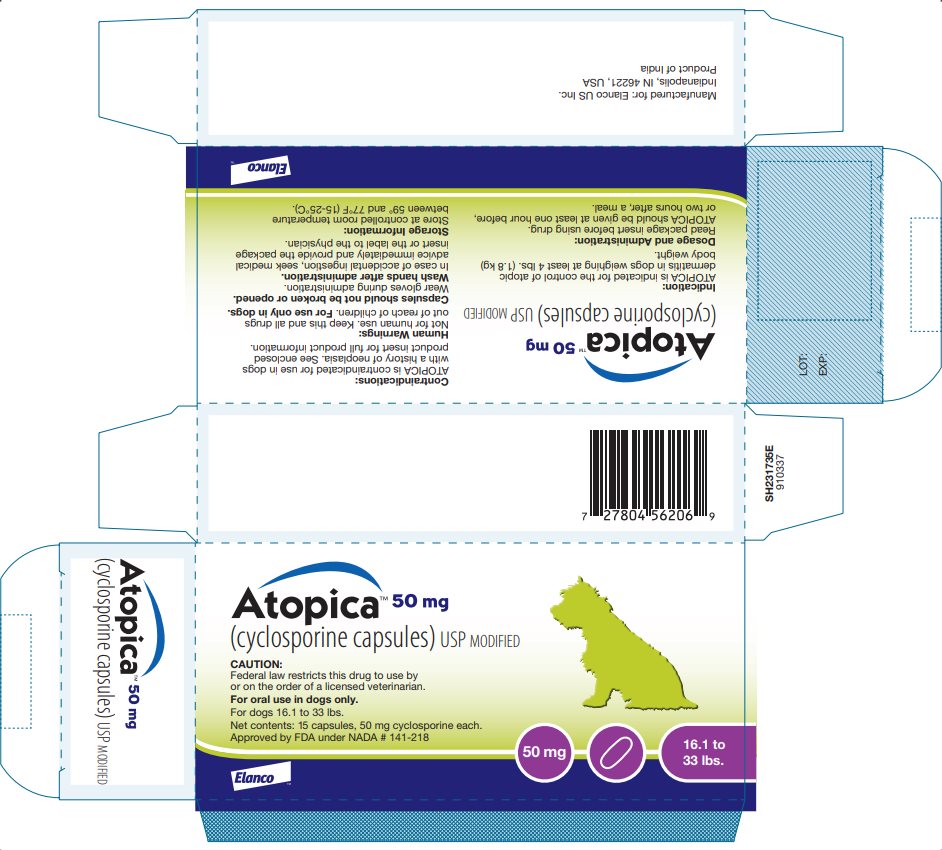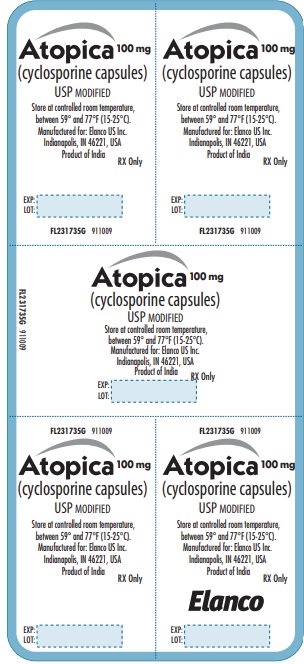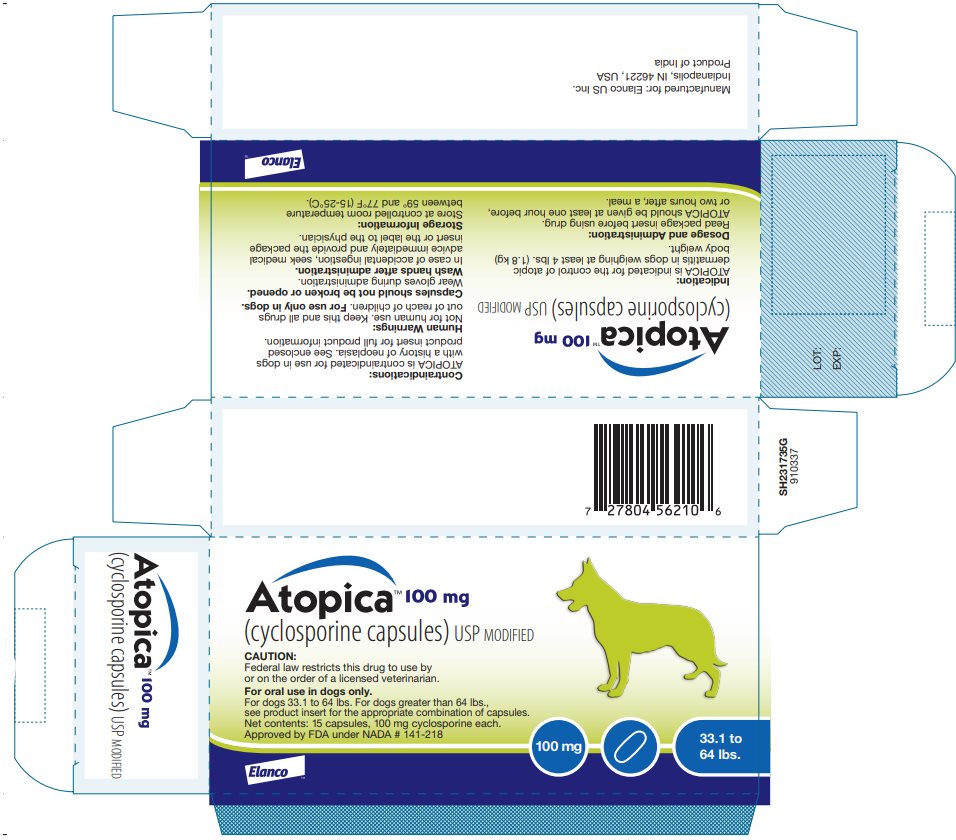 DRUG LABEL: Atopica
NDC: 58198-4351 | Form: CAPSULE, GELATIN COATED
Manufacturer: Elanco US Inc.
Category: animal | Type: PRESCRIPTION ANIMAL DRUG LABEL
Date: 20260220

ACTIVE INGREDIENTS: cyclosporine 10 mg/1 1

Atopica™

(cyclosporine capsules) USP MODIFIED

Caution:

Federal law restricts this drug to use by or on the order of a licensed veterinarian.

Keep this and all drugs out of reach of children.

Description:

ATOPICA (cyclosporine capsules) USP MODIFIED is an oral form of cyclosporine that immediately forms a microemulsion in an aqueous environment. Cyclosporine, the active ingredient in ATOPICA, is a cyclic polypeptide, immune modulating agent consisting of 11 amino acids. It is produced as a metabolite by the fungal species Beauveria nivea.

Chemically, cyclosporine A is designated Cyclo[[(E)-(2S,3R,4R)-3-hydroxy-4-methyl-2-(methylamino)-6-octenoyl]-L-2-aminobutyryl-N-methylglycyl-N-methyl-L-leucyl-L-valyl-N-methyl-L-leucyl-L-alanyl-D-ananyl-N-methyl-L-leucyl-N-methyl-L-leucyl-N-methyl-L-valyl].

The structural formula is:

Indications:

ATOPICA is indicated for the control of atopic dermatitis in dogs weighing at least 4 lbs. (1.8 kg) body weight.

Dosage and Administration:

The initial dose of ATOPICA is 5 mg/kg/day (3.3-6.7 mg/kg/day) as a single daily dose for 30 days. Following this initial daily treatment period, the dose of ATOPICA may be tapered by decreasing the frequency of dosing to every other day or twice weekly, until a minimum frequency is reached which will maintain the desired therapeutic effect. ATOPICA should be given at least one hour before or two hours after a meal. If a dose is missed, the next dose should be administered (without doubling) as soon as possible, but dosing should be no more frequent than once daily.

Dose Administration
Dog body; weight (lbs) | Dog body; weight (kg) | Dose; 5 mg/kg
4 – 6.5 lbs | 2 – 2.9 kg | 10 mg capsule
6.6 – 9 lbs | 3 – 3.9 kg | 2 x 10 mg capsules
9.1 – 16 lbs | 4 – 7.9 kg | 25 mg capsule
16.1 – 33 lbs | 8 – 14.9 kg | 50 mg capsule
33.1 – 64 lbs | 15 – 28.9 kg | 100 mg capsule
64.1 – 79 lbs | 29 – 35.9 kg | 100 mg capsule +50 mg capsule
79.1 – 121 lbs | 36 – 55.9 kg | 2 x 100 mg capsules

Contraindications:

ATOPICA is contraindicated for use in dogs with a history of neoplasia. Do not use in dogs with a hypersensitivity to cyclosporine.

Warnings:

ATOPICA (cyclosporine) is a systemic immunosuppressant that may increase the susceptibility to infection and the development of neoplasia.

Human Warnings:

Not for human use. Keep this and all drugs out of reach of children.

For use only in dogs.

Capsules should not be broken or opened. Wear gloves during administration.

Wash hands after administration. In case of accidental ingestion, seek medical advice immediately and provide the package insert or the label to the physician.

Precautions:

The safety and effectiveness of ATOPICA has not been established in dogs less than 6 months of age or less than 4 lbs body weight. ATOPICA is not for use in breeding dogs, pregnant or lactating bitches.

As with any immunomodulation regimen, exacerbation of sub-clinical neoplastic and infectious conditions may occur.

Gastrointestinal problems and gingival hyperplasia may occur at the initial recommended dose (See Animal Safety).

ATOPICA may cause elevated levels of serum glucose, and should be used with caution in cases with diabetes mellitus. If signs of diabetes mellitus develop following the use of ATOPICA, consideration should be given to tapering or discontinuing the dose.

ATOPICA should be used with caution with drugs that affect the P-450 enzyme system. Simultaneous administration of ATOPICA with drugs that suppress the P-450 enzyme system, such as azoles (e.g. ketoconazole), may lead to increased plasma levels of cyclosporine.

Since the effect of cyclosporine use on dogs with compromised renal function has not been studied, ATOPICA should be used with caution in dogs with renal insufficiency.

There have been reports of convulsions in human adult and pediatric patients receiving cyclosporine, particularly in combination with high dose methylprednisolone (See Animal Safety).

Killed vaccines are recommended for dogs receiving ATOPICA because the impact of cyclosporine on the immune response to modified live vaccines is unknown (See Animal Safety).

Adverse Reactions:

A total of 265 dogs were included in the field study safety analysis. One hundred and eleven (111) dogs were treated with placebo for the first 30 days. For the remainder of the study, all dogs received ATOPICA capsules.

Fourteen dogs withdrew from the study due to adverse reactions. Four dogs withdrew from the study after vomiting. One dog each withdrew from the study after diarrhea; vomiting, diarrhea and pruritus; vomiting, depression and lethargy; lethargy, anorexia and hepatitis; gingival hyperplasia, lethargy, polyuria/polydipsia and soft stool; seizure; sebaceous cyst; pruritus; erythema; or otitis externa.

Vomiting and diarrhea were the most common adverse reactions occurring during the study. In most cases, signs spontaneously resolved with continued dosing. In other cases, temporary dose modifications (brief interruption in dosing, divided dosing, or administration with a small amount of food) were employed to resolve signs.

Persistent otitis externa, urinary tract infections, anorexia, gingival hyperplasia, lymphadenopathy and lethargy were the next most frequent adverse events observed. Gingival hyperplasia regressed with dose tapering. Owners of four dogs reported seizures while dogs were receiving ATOPICA. In one dog, seizures were the result of a brain tumor diagnosed one month into the study. Another dog experienced seizures before and after the study.

Otitis externa, allergic otitis, or pinna erythema, with or without exudates, commonly accompanies atopy. Many dogs entered the study with otitis externa, which did not resolve without otic treatment. New cases of otitis externa, allergic otitis, or pinna erythema developed while dogs were receiving ATOPICA. However, the incidence rate was lower with ATOPICA compared to placebo. A change in the dose frequency was not necessary when new cases occurred.

Number of Dogs Displaying Each Clinical Observation in the Field Study
Clinical Sign | % out of 265
Vomiting | 30.9%
Diarrhea | 20.0%
Persistent Otitis Externa | 6.8%
Urinary Tract Infection | 3.8%
Anorexia | 3.0%
Lethargy | 2.3%
Gingival Hyperplasia | 2.3%
Lymphadenopathy | 2.3%

The following clinical signs were reported in less than 2% of dogs treated with ATOPICA in the field study: constipation, flatulence, Clostridial organisms in the feces, nausea, regurgitation, polyuria/polydipsia, strong urine odor, proteinuria, pruritus, erythema/flushed appearance, pyoderma, sebaceous adenitis, crusty dermatitis, excessive shedding, coarse coat, alopecia, papillomas, histiocytoma, granulomatous mass or lesion, cutaneous cyst, epulis, benign epithelial tumor, multiple hemangioma, raised nodule on pinna, seizure, shaking/trembling, hind limb twitch, panting, depression, irritability, hyperactivity, quieter, increased light sensitivity, reluctance to go outside, weight loss, hepatitis.

The following clinical signs were observed in 1.5-4.5% of dogs while receiving the placebo: vomiting, diarrhea and urinary tract infection. The following clinical signs were observed in less than 1% of dogs receiving the placebo: anorexia, otitis externa, cutaneous cysts, corneal opacity, lymphadenopathy, erythema/flushed appearance.

Clinical Pathology Changes: During the study, some dogs experienced changes in clinical chemistry parameters while receiving ATOPICA, as described in the following table:

Clinical Chemistry | % Affected; (out of 265)
Elevated Creatinine | 7.8%
Hyperglobulinemia | 6.4%
Hyperphosphatemia | 5.3%
Hyperproteinemia | 3.4%
Hypercholesterolemia | 2.6%
Hypoalbuminemia | 2.3%
Hypocalcemia | 2.3%
Elevated BUN | 2.3%

In addition, the following changes in clinical chemistry parameters were noted in less than 2% of dogs: hypernatremia; hyperkalemia, elevated ALT, elevated ALP, hypercalcemia and hyperchloremia. These clinical pathology changes were generally not associated with clinical signs.

Post-approval Experience: (Rev 2014)

The following adverse events are based on post-approval adverse drug experience reporting. Not all adverse reactions are reported to FDA CVM. It is not always possible to reliably estimate the adverse event frequency or establish a causal relationship to product exposure using this data. The following adverse events are grouped by body system and are presented in decreasing order of reporting frequency.

Gastrointestinal: Emesis, diarrhea, gingival hyperplasia, hemorrhagic diarrhea, abdominal pain, hematemesis, digestive tract hemorrhage, hypersalivation, retching, flatulence, tenesmus, intestinal stasis, digestive tract hypermotility, melena, pancreatitis, involuntary defecation

General: Lethargy, anorexia, weight loss, polydipsia, hyperthermia, pale mucous membrane, general pain, collapse, dehydration, edema

Dermatologic: Pruritus, dermatitis and eczema, alopecia, erythema, papilloma, bacterial skin infection, skin lesion, skin and/or appendage neoplasm, pigmentation disorder, hair change, hyperkeratosis, histiocytoma, fungal skin infection, dermal cyst(s), desquamation

Behavioral: Hyperactivity, behavioral changes, anxiety, vocalization, aggression, inappropriate urination, disorientation

Neurologic: Muscle tremor, convulsion, ataxia, paresis

Respiratory: Tachypnea, dyspnea, cough

Urologic: Polyuria, urine abnormalities (hematuria, urinary tract infection, proteinuria, glucosuria, decreased urine concentration) urinary incontinence, cystitis, renal failure, renal insufficiency

Immune: Urticaria, anaphylaxis, allergic edema

Blood and lymphatic: Lymphadenopathy, anemia, hypoalbuminemia, leukopenia

Hepatic: Elevated Liver Enzymes, hepatopathy, hepatomegaly, hepatitis

Musculoskeletal: Lameness, limb weakness, myositis

Ear and labyrinth: Otitis externa

Cardio-vascular: Tachycardia

Endocrine: Diabetes mellitus, hyperglycemia

In some cases, death/euthanasia has been reported as an outcome of the adverse events listed above.

Neoplasms have been reported in dogs taking ATOPICA, including reports of lymphoma/lymphosarcoma and mast cell tumor. It is unknown if these were preexisting or developed de novo while on ATOPICA.

Diabetes mellitus has been reported; West Highland White Terriers are the most frequently reported breed.

Contact Information:

To report suspected adverse drug events or for technical assistance, contact Elanco US Inc. 1-888-545-5973. For additional information about adverse drug experience reporting for animal drugs, contact FDA at 1-888-FDA-VETS or http://www.fda.gov/reportanimalae

Clinical Pharmacology:

Cyclosporine is an immunosuppressive agent that has been shown to work via suppression of T-helper and T-suppressor cells and inhibition of interleukin-2.

It does not depress hematopoesis or the function of phagocytic cells.

A decrease in CD4 and CD8 cells was not seen in dogs receiving 20 mg/kg/day of cyclosporine for 56 days. ATOPICA is not a corticosteroid or an antihistamine.

Metabolism:

Cyclosporine is extensively metabolized by the cytochrome P-450 enzyme system in the liver, and to a lesser degree in the gastrointestinal tract and the kidney. The metabolism of cyclosporine can be altered by the co-administration of a variety of agents (See Precautions).

Effectiveness Field Study:

A multisite, placebo controlled, double masked, field study was conducted in the United States and Canada using 16 investigators. Two hundred sixty five (265) dogs aged 1-10 years, weighing 4-121 lbs received either ATOPICA capsules at 5 mg/kg/day or placebo capsules. After 30 days, placebo dogs were switched to ATOPICA capsules.

Dogs were treated with ATOPICA capsules for a total of 4 months. No additional therapy with antihistamines, corticosteroids or medicated shampoos was permitted.

Evaluations for pruritus and for skin lesions to derive a Canine Atopic Dermatitis Extent and Severity Index (CADESI) score occurred at enrollment and at monthly intervals. One hundred ninety-two (192) dogs were included in the statistical analysis of effectiveness.

At the end of the 30 day placebo controlled period, CADESI scores of dogs treated with ATOPICA capsules improved by 45% from enrollment, while CADESI scores of dogs treated with placebo worsened by 9%. Seventy-four percent (74%) of ATOPICA treated dogs showed improvement in their pruritus scores over the first 30 day period, while only 24% of the placebo treated dogs showed an improvement. Owner and Veterinary Global Assessment in response to treatment also demonstrated statistically significant (p<0.0001) improvement. After 4 weeks of therapy, Owner and Veterinary Global Assessments showed approximately twice as much improvement in the ATOPICA treated dogs as compared to placebo treated dogs.

Improvements in pruritus accompanied by 50% or 75% improvements in CADESI scores resulted in dose reductions to every other day or twice weekly respectively. Not all dogs were able to decrease to twice weekly dosing. Some animals required upward or downward dosage adjustments during the study. Such adjustments should be expected during therapy of this disease. Dogs unable to decrease from once daily dosing after 60 days were considered dose reduction failures for the purposes of the study.

The results of dose assignments, based on the study criteria, for each 4-week dosing period, are shown in the graph.

Analysis of blood levels of cyclosporine drawn during the study demonstrated no correlation between blood cyclosporine levels and CADESI scores or pruritus; therefore monitoring blood cyclosporine levels is not an appropriate predictor of effectiveness.

Animal Safety:

In a 52-week oral study with dose levels of 0, 1, 3, and 9 times the target initial daily dose, emesis, diarrhea and weight loss were seen in all cyclosporine treated groups with increasing frequency as the dose increased.

Multilocular papilloma-like lesions of the skin were observed in 5 out of 8 high dose animals between weeks 20 and 40. These changes regressed spontaneously after drug was withdrawn.

Other findings in the mid and high dose animals included swollen gums due to chronic gingivitis and periodontitis, lower serum albumin and higher cholesterol, triglyceride, IgA and IgG. Hematological findings consisted of anemia and decreased leukocyte counts in a few high dose animals. Erythrocyte sedimentation rates were increased at all dose levels in a dose dependent fashion. Notable histopathological findings were limited to lymphoid atrophy, hypertrophic gums (from gingivitis) and slight regenerative changes of the renal tubular epithelium in high dose animals. The findings were shown to be reversible during a 12-week recovery phase of the study.

In a 90-day study with ATOPICA, dogs were dosed in one of two patterns: either 1, 3, or 5X the maximum recommended target initial daily dose for 90 days, or 1, 3, or 5X the maximum recommended target initial daily dose for 30 days followed by tapering to mimic the recommended clinical dosing pattern. The maximum recommended dose, when administered for 90 days causes callus-like lesions on the footpads, red/swollen pinnae, mild to moderate gingival proliferation, hyperkeratotic areas on the integument, hair loss, salivation, vomiting, and diarrhea/abnormal stools. These clinical signs lessened in severity or resolved as the drug was tapered to a lower dose. Increased erythrocyte sedimentation rate, hyperproteinemia, hyperglobulinemia, hypoalbuminemia, hypocalcemia, hypophosphatemia, and hypomagnesemia were observed at three and five times the maximum recommended dose. These resolved as the dose was tapered.

When administered at higher than the maximum recommended dose, raised skin lesions, papilloma-like areas on the integument, popliteal lymph node enlargement, and weight loss were also seen. There were no ATOPICA related changes in urinalysis, ECG, blood pressure, or ophthalmologic exams.

Gross necropsy revealed epithelial changes consistent with those seen on physical examination. Proliferation of gingiva and toe pad epithelium was seen in all ATOPICA dosed groups, and was seen in a dose dependent fashion. The degree of the proliferation was greater in dogs in the non-tapered groups as compared to the tapered groups. Similar changes were noted on histopathologic examination of the cutaneous changes seen on physical examination. These lesions were characterized by epidermal hyperplasia, chronic dermatitis and hyperkeratosis.

Methylprednisolone combination: Twenty-four dogs were administered 1 mg/kg/day methylprednisolone alone for 14 days followed by 20 mg/kg/day cyclosporine either alone or in combination with methylprednisolone, or placebo for 14 days. There was no evidence of seizures/convulsions or neurological signs.

Vaccination effect: The effect of ATOPICA administration on the immunological response to vaccination was evaluated in a study in which 16 dogs were dosed with either ATOPICA at 20 mg/kg/day (4X the initial daily dose) or placebo for 56 days. All dogs were vaccinated on Day 27 with a killed commercial rabies virus and a multivalent vaccine (DHLPP) which included a modified live virus. Antibody titers for rabies, canine distemper, canine adenovirus type 2, parainfluenza, parvovirus, Leptospira canicola, and Leptospira icterohaemmorrhagiae were examined on Days 0, 27 (prior to vaccination), 42 and 56. Quantification of CD4, CD8, and CD3 T-lymphocytes was analyzed.

Clinical changes included soft stool and dermatologic changes consistent with those seen in previous studies. Antibody titers did not rise in dogs treated with ATOPICA or the placebo for any component of the multivalent vaccine which included a modified live virus while all animals demonstrated a significant increase in antibody rabies titer by Day 42 or 15 days post-revaccination. No effect was seen on T-lymphocytes.

Storage Conditions:

ATOPICA should be stored and dispensed in the original unit-dose container at controlled room temperature between 59° and 77°F (15-25°C).

How Supplied:

ATOPICA soft gelatin capsules (cyclosporine capsules) USP MODIFIED are supplied in packages of 15 unit-dose blisters as follows:

10 mg: oval, white capsules imprinted with red “NVR 10”.
25 mg: oval, blue-gray capsules imprinted with red “NVR 25mg”.
50 mg: oval, white capsules imprinted with red “NVR 50mg”.
100 mg: oval, blue-gray capsules imprinted with red “NVR 100mg”.

Manufactured for: Elanco US Inc.
Indianapolis, IN 46221, USA

Approved by FDA under NADA # 141-218

Revision Date: November 2025

Atopica, Elanco and the diagonal bar logo are trademarks of Elanco or its affiliates.

© 2025 Elanco or its affiliates

A161259

Elanco™

Principal Display Panel - Atopica 10mg Blister Label

Atopica 10 mg

(cyclosporine capsules)

USP MODIFIED

Store at controlled room temperature,
between 59° and 77°F (15-25°C).

Manufactured for: Elanco US Inc.

Indianapolis, IN 46221, USA

Product of India

RX Only

EXP:

LOT:

FL231735A 911009

Principal Display Panel - Atopica 10mg Carton Label

Atopica™ 10 mg

(cyclosporine capsules) USP MODIFIED

CAUTION:

Federal law restricts this drug to use by
or on the order of a licensed veterinarian.

For oral use in dogs only.

For dogs 4 to 9 lbs.

Net contents: 15 capsules, 10 mg cyclosporine each.

Approved by FDA under NADA # 141-218

10 mg

4 to 9 lbs.

Elanco™

Principal Display Panel - Atopica 25mg Blister Label

Atopica 25 mg

(cyclosporine capsules)

USP MODIFIED

Store at controlled room temperature,
between 59° and 77°F (15-25°C).

Manufactured for: Elanco US Inc.

Indianapolis, IN 46221, USA

Product of India

RX Only

EXP:

LOT:

FL231735C 911009

Principal Display Panel - Atopica 25mg Carton Label

Atopica™ 25 mg

(cyclosporine capsules) USP MODIFIED

CAUTION:

Federal law restricts this drug to use by
or on the order of a licensed veterinarian.

For oral use in dogs only.

For dogs 9.1 to 16 lbs.

Net contents: 15 capsules, 25 mg cyclosporine each.

Approved by FDA under NADA # 141-218

25 mg

9.1 to 16 lbs.

Elanco™

Principal Display Panel - Atopica 50mg Blister Label

Atopica 50 mg

(cyclosporine capsules)

USP MODIFIED

Store at controlled room temperature,
between 59° and 77°F (15-25°C).

Manufactured for: Elanco US Inc.

Indianapolis, IN 46221, USA

Product of India

RX Only

EXP:

LOT:

FL231735E 911009

Principal Display Panel - Atopica 50mg Carton Label

Atopica™ 50 mg

(cyclosporine capsules) USP MODIFIED

CAUTION:

Federal law restricts this drug to use by
or on the order of a licensed veterinarian.

For oral use in dogs only.

For dogs 16.1 to 33 lbs.

Net contents: 15 capsules, 50 mg cyclosporine each.

Approved by FDA under NADA # 141-218

50 mg

16.1 to 33 lbs.

Elanco™

Principal Display Panel - Atopica 100mg Blister Label

Atopica 100 mg

(cyclosporine capsules)

USP MODIFIED

Store at controlled room temperature,
between 59° and 77°F (15-25°C).

Manufactured for: Elanco US Inc.

Indianapolis, IN 46221, USA

Product of India

RX Only

EXP:

LOT:

FL231735G 911009

Principal Display Panel - Atopica 100mg Carton Label

Atopica™ 100 mg

(cyclosporine capsules) USP MODIFIED

CAUTION:

Federal law restricts this drug to use by
or on the order of a licensed veterinarian.

For oral use in dogs only.

For dogs 33.1 to 64 lbs. For dogs greater than 64 lbs.,
see product insert for the appropriate combination of capsules.

Net contents: 15 capsules, 100 mg cyclosporine each.

Approved by FDA under NADA # 141-218

100 mg

33.1 to 64 lbs.

Elanco™